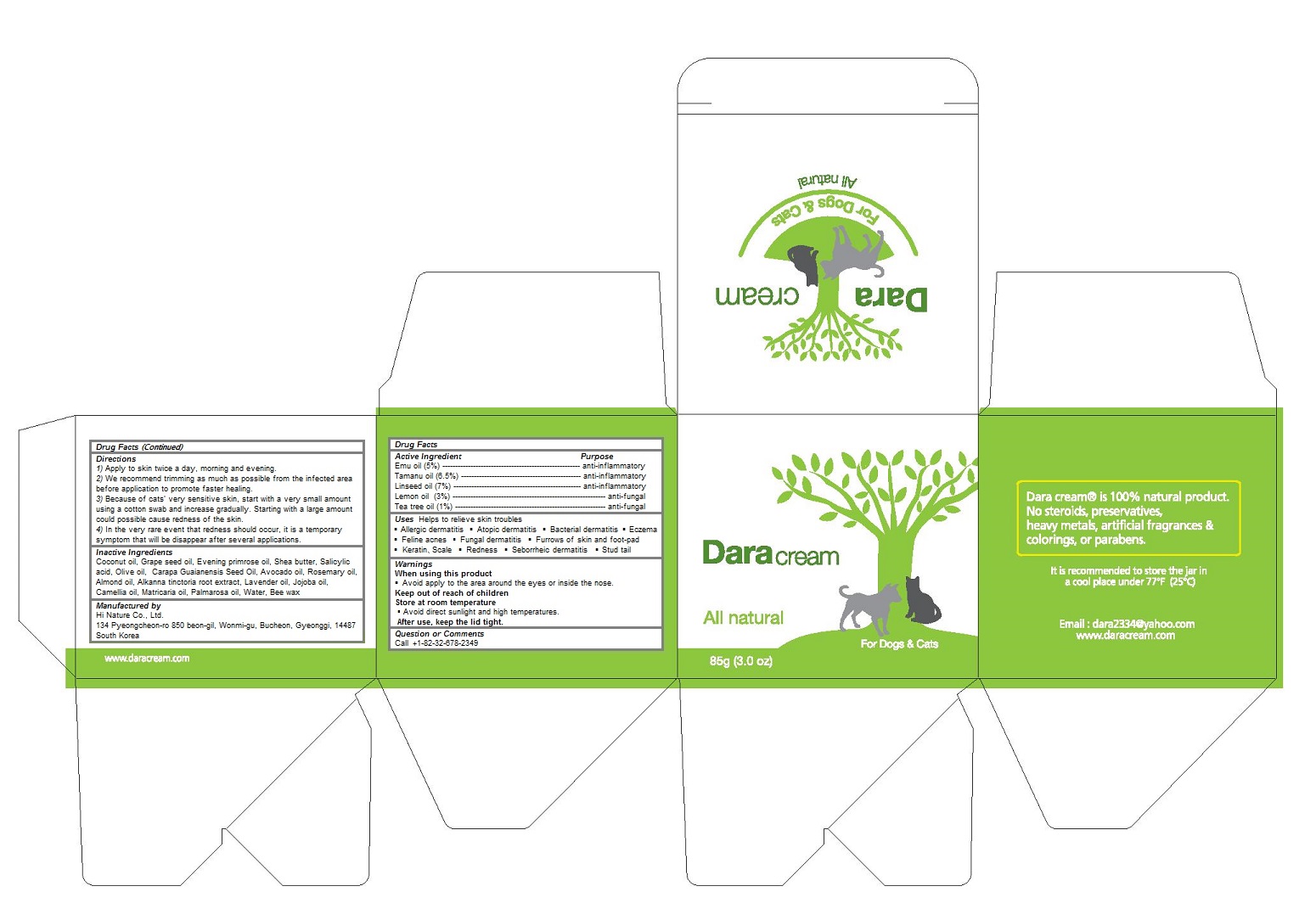 DRUG LABEL: Dara Cream (85g)
NDC: 86068-102 | Form: CREAM
Manufacturer: Hi Nature Co., Ltd.
Category: animal | Type: OTC ANIMAL DRUG LABEL
Date: 20160708

ACTIVE INGREDIENTS: LEMON OIL 0.03 1/85 g; EMU OIL 0.05 1/85 g; TEA TREE OIL 0.01 1/85 g; TAMANU OIL 0.065 1/85 g; LINSEED OIL 0.07 1/85 g
INACTIVE INGREDIENTS: COCONUT OIL; GRAPE SEED OIL; EVENING PRIMROSE OIL; SHEA BUTTER; SALICYLIC ACID; OLIVE OIL; CARAPA GUIANENSIS SEED OIL; AVOCADO OIL; ROSEMARY OIL; ALMOND OIL; ALKANNA TINCTORIA ROOT; LAVENDER OIL; JOJOBA OIL; CAMELLIA OIL; CHAMOMILE FLOWER OIL; PALMAROSA OIL; water; YELLOW WAX

Dara Cream (85g)